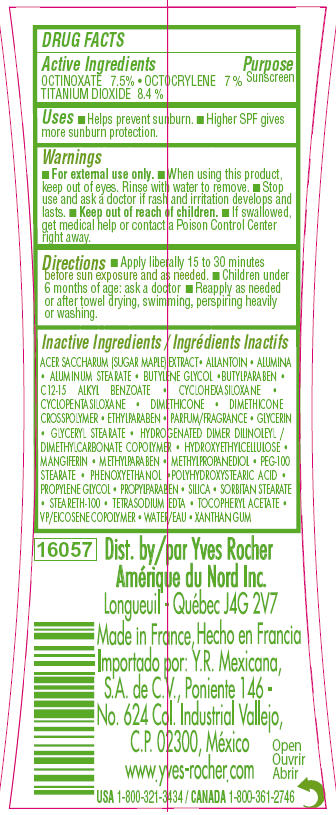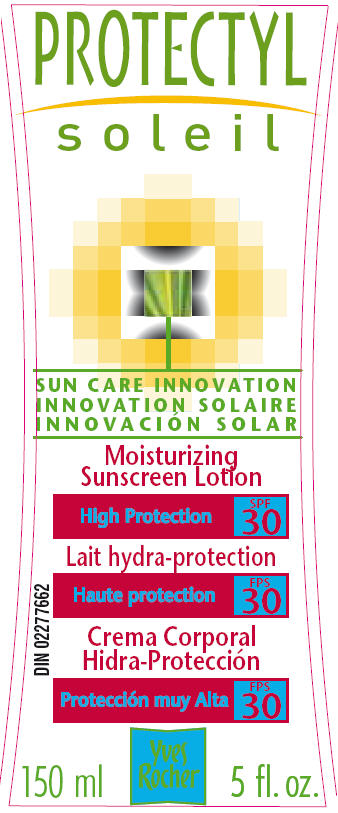 DRUG LABEL: Protectyl soleil moisturizing sunscreen lotion high protection spf 30
NDC: 63505-156 | Form: LOTION
Manufacturer: Yves Rocher North America Inc
Category: otc | Type: HUMAN OTC DRUG LABEL
Date: 20110428

ACTIVE INGREDIENTS: OCTINOXATE  7.5 mL/100 mL; OCTOCRYLENE 7.0 mL/100 mL; TITANIUM DIOXIDE 8.4 mL/100 mL
INACTIVE INGREDIENTS: ACER SACCHARUM BARK/SAP; ALLANTOIN; ALUMINUM OXIDE; ALUMINUM STEARATE; BUTYLENE GLYCOL; BUTYLPARABEN; ALKYL (C12-15) BENZOATE; CYCLOMETHICONE 6; CYCLOMETHICONE 5; DIMETHICONE; ETHYLPARABEN; GLYCERIN; GLYCERYL MONOSTEARATE; HYDROXYETHYL CELLULOSE (5000 CPS AT 1%); MANGIFERIN; METHYLPARABEN ; METHYLPROPANEDIOL; PEG-100 STEARATE; PHENOXYETHANOL; POLYHYDROXYSTEARIC ACID (2300 MW); PROPYLENE GLYCOL; PROPYLPARABEN ; SILICON DIOXIDE ; SORBITAN MONOSTEARATE; STEARETH-100; EDETATE SODIUM; .ALPHA.-TOCOPHEROL ACETATE, D-; WATER; XANTHAN GUM 

ACTIVE INGREDIENT

Actives ingredients
Octinoxate 7.5%
Octocrylene 7.0%
Titanium dioxide 8.4%

Purpose
Sunscreen

Keep out of reach of children. If swallowed, get medical help or contact a Poison Control Center right away.

Uses
Helps prevent sunburn. Higher SPF gives more sunburn protection.

Warnings:
For external use only. When using this product, keep out of eyes. Rinse with water to remove.
Stop use and ask a doctor if rash and irritation develops and lasts.

Directions:
Apply liberally 15 to 30 minutes before sun exposure and as needed. Reapply as needed
or after towel drying, swimming, perspiring heavily or washing.

ASK DOCTOR

Children under 6 months of age: ask a doctor.

Inactive ingredients:
ACER SACCHARINUM (SUGAR MAPLE) EXTRACT - ALLANTOIN - ALUMINA - ALUMINUM STEARATE - BUTYLENE GLYCOL - BUTYLPARABEN - C12-15 ALKYL BENZOATE - CYCLOHEXASILOXANE - CYCLOPENTASILOXANE - DIMETHICONE - DIMETHICONE CROSSPOLYMER - ETHYLPARABEN - FRAGRANCE (PARFUM) - GLYCERIN - CLYCERYL STEARATE - HYDROGENATED DIMER DILINOLEYL / DIMETHYLCARBONATE COPOLYMER - HUDROXYETHYLCELLULOSE - MANGIFERIN - METHYLPARABEN - METHYLPROPANEDIOL - PEG-100 STEARATE - PHENOXYETHANOL - POLYHYDROXYSTEARIC ACID - PROPYLENE GLYCOL - PROPYLPARABEN - SILICA - SORBITAN STEARATE - STEARETH-100 - TETRASODIUM EDTA - TOCOPHERYL ACETATE - VP/EICOSENE COPOLYMER - WATER (AQUA) - XANTHAN GUM

PACKAGE LABEL

Protectyl Soleil

Moisturizing Sunscreen Lotion
High Protection SPF30

150 ml 5 fl.oz.